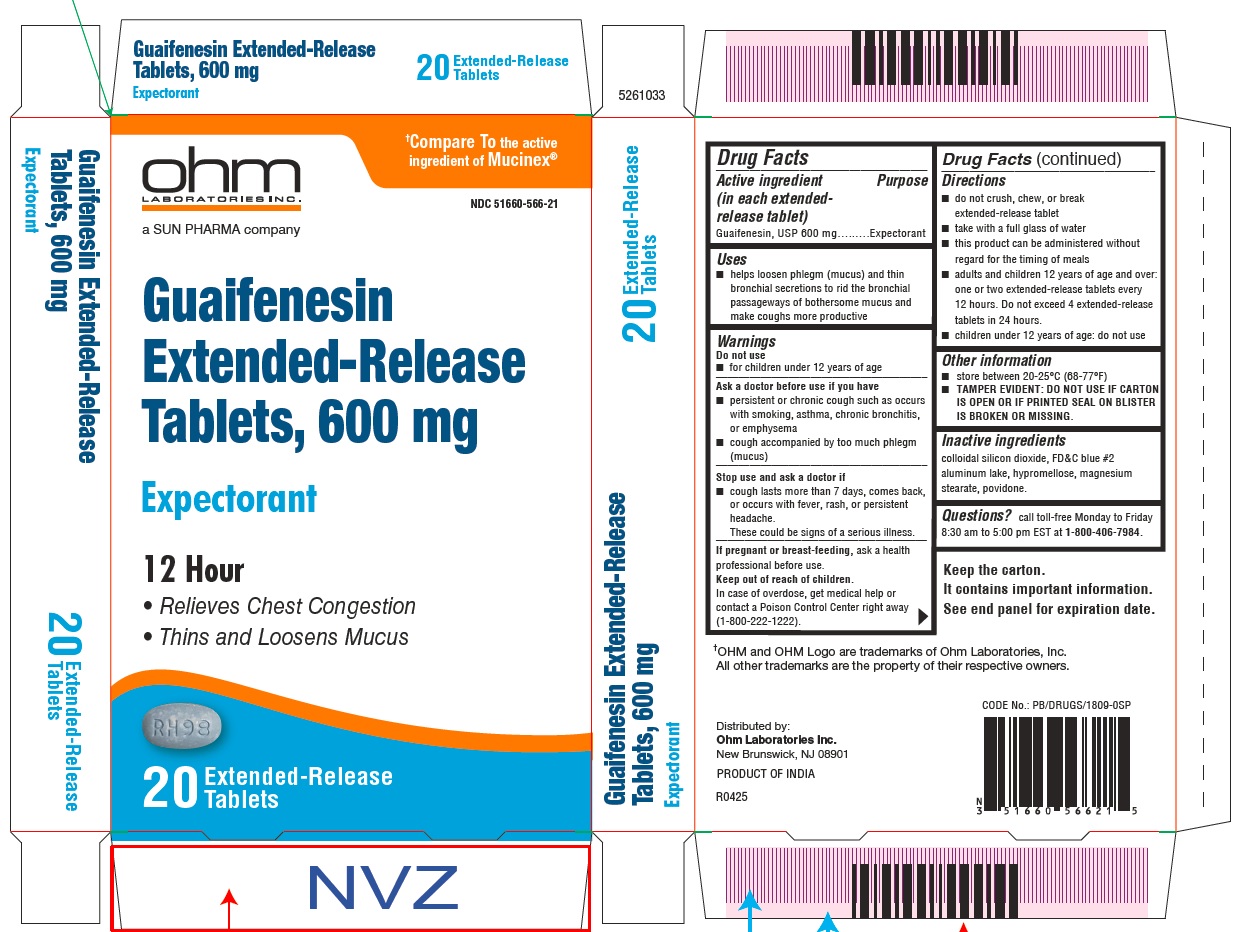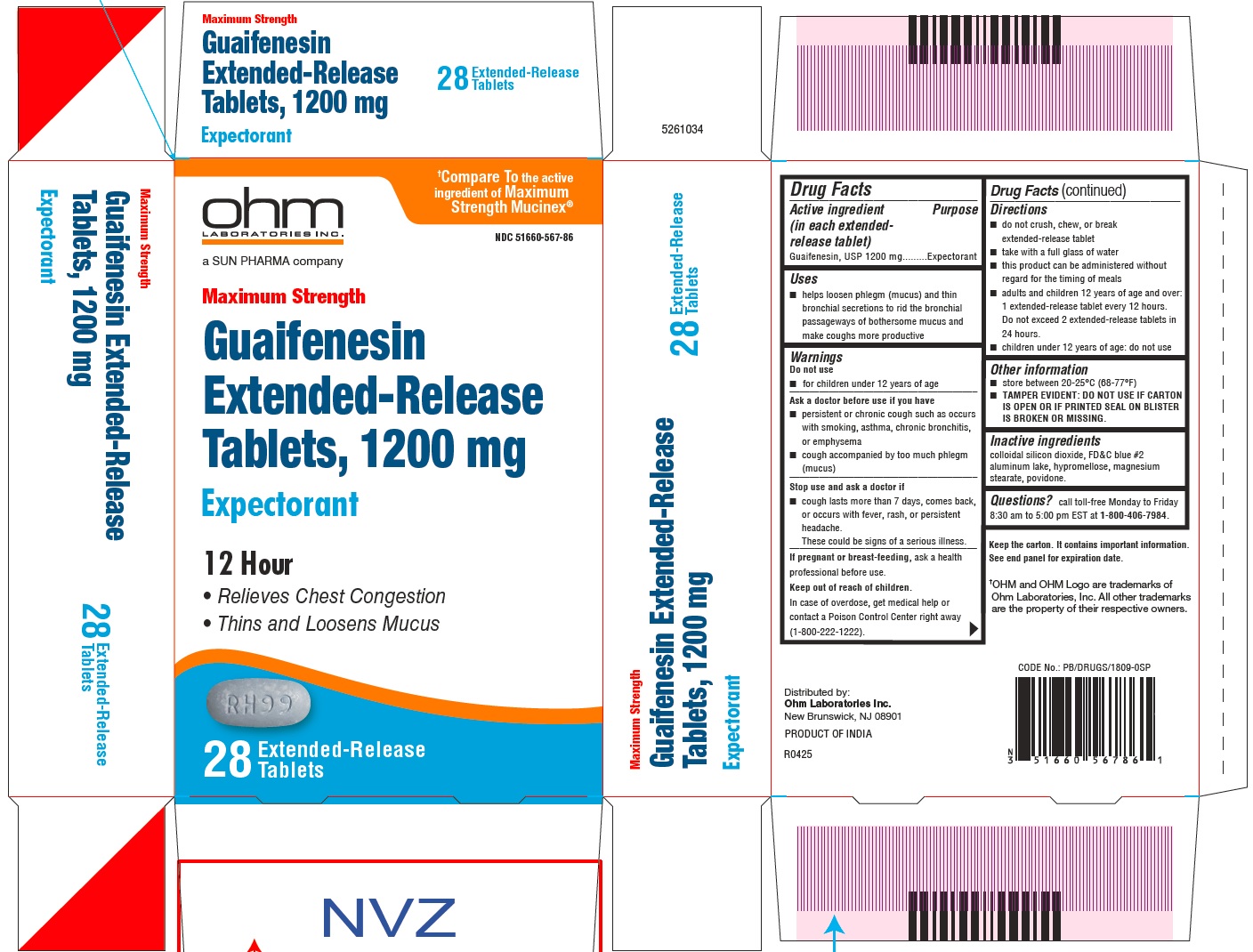 DRUG LABEL: Guaifenesin
NDC: 51660-566 | Form: TABLET, EXTENDED RELEASE
Manufacturer: Ohm Laboratories, Inc.
Category: otc | Type: HUMAN OTC DRUG LABEL
Date: 20260212

ACTIVE INGREDIENTS: GUAIFENESIN 600 mg/1 1
INACTIVE INGREDIENTS: SILICON DIOXIDE; FD&C BLUE NO. 2; HYPROMELLOSE, UNSPECIFIED; MAGNESIUM STEARATE; POVIDONE, UNSPECIFIED

Drug Facts

Active ingredient

(in each extended-release tablet)

Guaifenesin, USP

Purpose

Expectorant

Keep Out of Reach of Children

In case of overdose, get medical help or contact a Poison Control Center right away (1-800-222-1222).

Uses

- Helps loosen phlegm (mucus) and thin bronchial secretions to rid the bronchial passageways of bronchial mucus and make coughs more productive

Warnings

Do not use

- for children under 12 years of age

Ask a doctor before use if you have

- persistent or chronic cough such as occurs with smoking, asthma, chronic bronchitis, or emphysema
- cough accompanied by too much phlegm (mucus)

Stop use and ask a doctor if

- cough lasts more than 7 days, comes back or occurs with fever, rash, or persistent headache.
- These could be signs of serious illness.

If pregnant or breast-feeding,ask a health professional before use.

Directions

- do not crush, chew or break extended-release tablet
- take with a full glass of water
- this product can be administered without regard for the timing of meals
- adults and children over 12 years of age and over: one or two extended-release tablets every 12 hours. Do not exceed 4 extended-release tablets in 24 hours.
- children under 12 years of age: do not use.

Other information

- store between 20-25°C (68-77°F)
- TAMPER EVIDENT: DO NOT USE IF CARTON IS OPEN OR IF PRINTED SEAL ON BLISTER IS BROKEN OR MISSING.

Inactive Ingredients

colloidal silicon dioxide, FD&C blue # 2, aluminum lake, hypromellose, magnesium stearate, povidone.

Questions

call toll-free Monday to Friday 8:30 am to 5:00 pm EST at 1-800-406-7984.

Keep the carton. It contains important information. See end panel for expiration date.

†OHM and OHM Logo are trademarks of Ohm Laboratories, Inc. All other trademarks are the property of their respective owners.

Distributed by:
Ohm Laboratories Inc.
New Brunswick, NJ 08901

PRODUCT OF INDIA

R0425

CODE No.: PB/DRUGS/1809-0SP